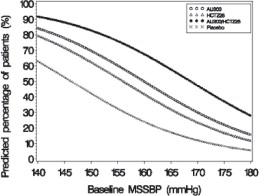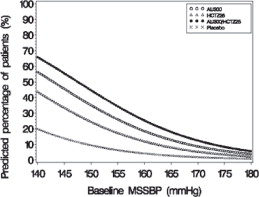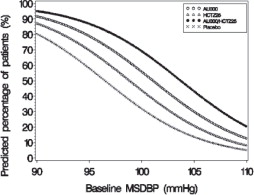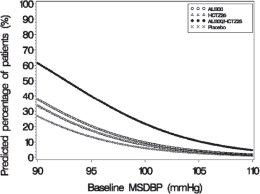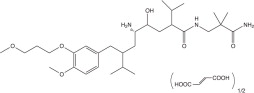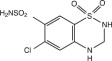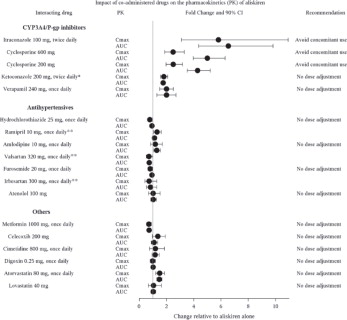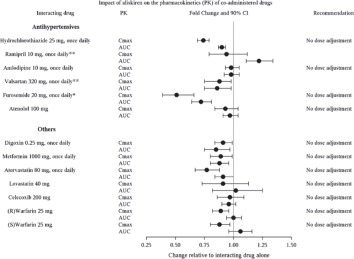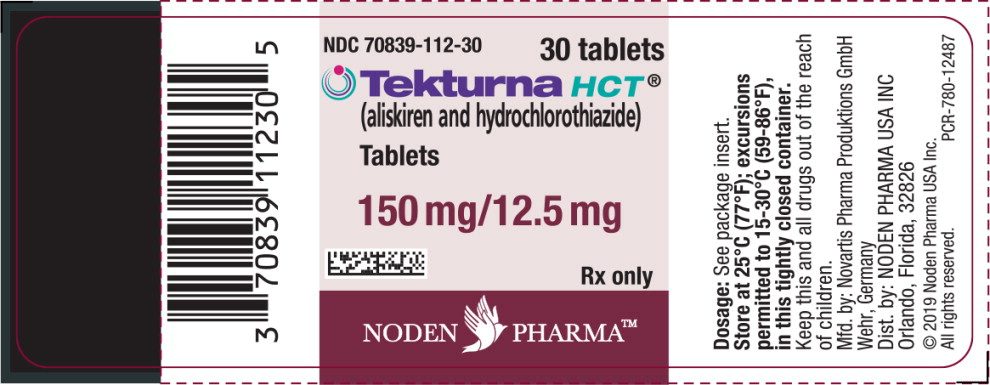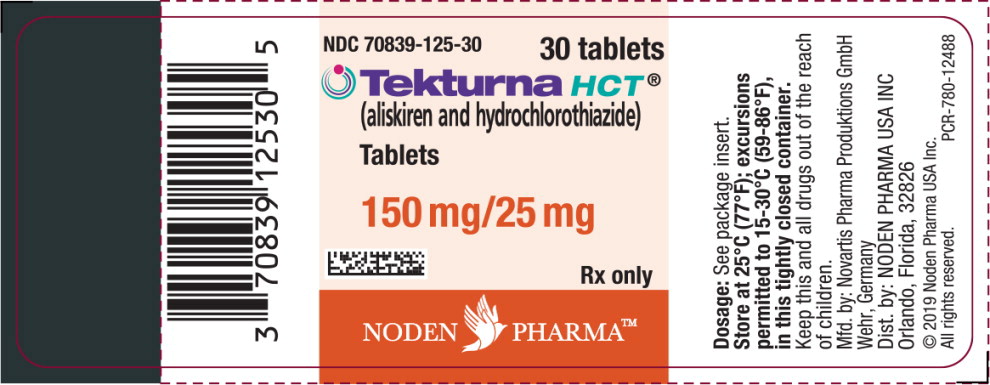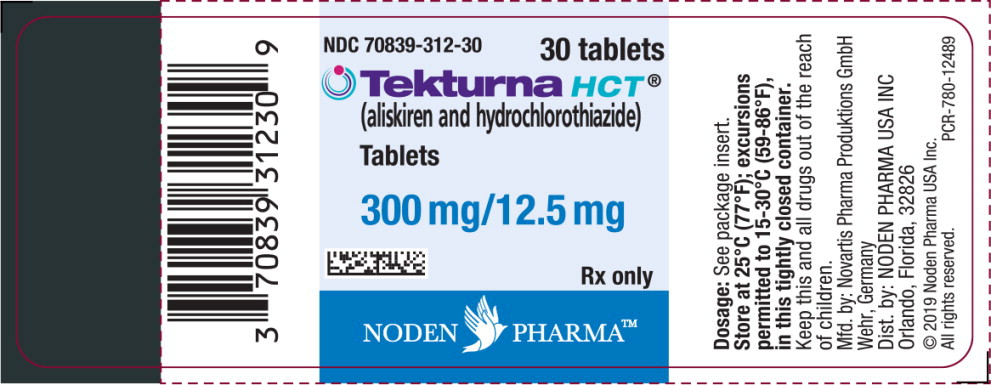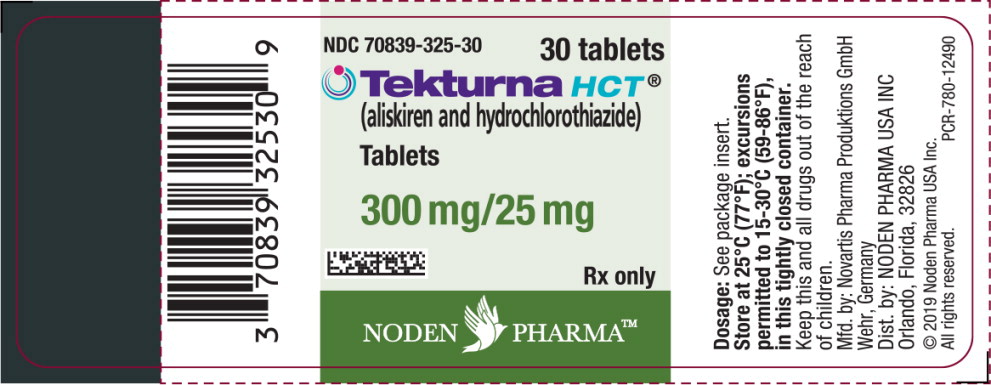 DRUG LABEL: Tekturna HCT
NDC: 70839-112 | Form: TABLET, FILM COATED
Manufacturer: Noden Pharma USA, Inc.
Category: prescription | Type: HUMAN PRESCRIPTION DRUG LABEL
Date: 20221116

ACTIVE INGREDIENTS: ALISKIREN HEMIFUMARATE 150 mg/1 1; HYDROCHLOROTHIAZIDE 12.5 mg/1 1
INACTIVE INGREDIENTS: SILICON DIOXIDE; CROSPOVIDONE (15 MPA.S AT 5%); HYPROMELLOSES; FERRIC OXIDE RED; LACTOSE, UNSPECIFIED FORM; MAGNESIUM STEARATE; CELLULOSE, MICROCRYSTALLINE; POLYETHYLENE GLYCOL, UNSPECIFIED; POVIDONE; TALC; TITANIUM DIOXIDE; STARCH, WHEAT

HIGHLIGHTS OF PRESCRIBING INFORMATION

These highlights do not include all the information needed to use TEKTURNA HCT safely and effectively. See full prescribing information for TEKTURNA HCT.
TEKTURNA® HCT (aliskiren and hydrochlorothiazide) tablets, for oral use
Initial U.S. Approval: 2008

RECENT MAJOR CHANGES

Contraindications (4) | 3/2015
Warnings and Precautions (5.1, 5.2, 5.5, 5.8) | 3/2015

WARNING: FETAL TOXICITY

See full prescribing information for complete boxed warning.

- When pregnancy is detected, discontinue Tekturna HCT as soon as possible. (5.1, 8.1)
- Drugs that act directly on the renin-angiotensin system can cause injury and death to the developing fetus. (5.1, 8.1)

1 INDICATIONS AND USAGE

Tekturna HCT is a combination of aliskiren, a renin inhibitor, and hydrochlorothiazide (HCTZ), a thiazide diuretic, indicated for the treatment of hypertension, to lower blood pressure:

- In patients not adequately controlled with monotherapy. (1)
- As initial therapy in patients likely to need multiple drugs to achieve their blood pressure goals. (1)

Lowering blood pressure reduces the risk of fatal and nonfatal cardiovascular events, primarily strokes and myocardial infarction.

2 DOSAGE AND ADMINISTRATION

- Initiate with 150/12.5mg daily. Titrate as needed up to a maximum of 300/25 mg (2.2)
- Order of increasing mean effect: 150/12.5 mg, 150/25 mg or 300/12.5 mg, and 300/25 mg (2.1)
- Replacement therapy: May be substituted for titrated components (2.4)

3 DOSAGE FORMS AND STRENGTHS

Tablets (mg aliskiren/mg HCTZ): 150/12.5, 150/25, 300/12.5, 300/25 (3)

4 CONTRAINDICATIONS

Do not use with angiotensin receptor blockers (ARBs) or angiotensin- converting enzyme inhibitors (ACEIs) in patients with diabetes. (4) Anuria (4)

Hypersensitivity to sulfonamide-derived drugs or to any of the components. (4)

5 WARNINGS AND PRECAUTIONS

- Avoid concomitant use with ARBs or ACEIs particularly in patients with renal impairment [creatinine clearance (CrCl) <60 mL/min]. (5.2, 5.4)
- Anaphylactic Reactions and Head and Neck Angioedema. (5.3)
- Hypotension: Correct imbalances in volume and/or salt-depleted patients. (5.4)
- Impaired Renal Function: Monitor serum creatinine periodically. (5.5)
- Hyperkalemia: Monitor potassium levels periodically. (5.8)
- Acute Myopia and Secondary Angle Closure Glaucoma. (5.10)

6 ADVERSE REACTIONS

The most common adverse reactions (incidence ≥1.5% and more common than with placebo) are: dizziness and diarrhea. (6.1)

To report SUSPECTED ADVERSE REACTIONS, contact Noden Pharma USA Inc. at 1-844-399-5701 or FDA at 1-800-FDA-1088

or www.fda.gov/medwatch.

7 DRUG INTERACTIONS

- Cyclosporine or Itraconazole: Avoid concomitant use. (5.9, 7, 12.3)
- Nonsteroidal Anti-inflammatory Drugs (NSAIDs): Increased risk of renal impairment and loss of antihypertensive effect. (7)
- Antidiabetic Drugs: Dosage adjustment of antidiabetic may be required. (7)
- Cholestyramine and Colestipol: Reduced absorption of thiazides. (7)
- Lithium: Increased risk of lithium toxicity when used with diuretics. (7)

8 USE IN SPECIFIC POPULATIONS

Lactation: Breastfeeding not recommended. (8.2)

FULL PRESCRIBING INFORMATION

WARNING: FETAL TOXICITY

- When pregnancy is detected, discontinue Tekturna HCT as soon as possible. (5.1, 8.1)
- Drugs that act directly on the renin-angiotensin system can cause injury and death to the developing fetus. (5.1, 8.1)

1 INDICATIONS AND USAGE

Tekturna HCT is indicated for the treatment of hypertension, to lower blood pressure. Lowering blood pressure reduces the risk of fatal and nonfatal cardiovascular events, primarily strokes and myocardial infarctions. These benefits have been seen in controlled trials of antihypertensive drugs from a wide variety of pharmacologic classes including hydrochlorothiazide (HCTZ). There are no controlled trials demonstrating risk reduction with Tekturna HCT.

Control of high blood pressure should be part of comprehensive cardiovascular risk management, including, as appropriate, lipid control, diabetes management, antithrombotic therapy, smoking cessation, exercise, and limited sodium intake. Many patients will require more than 1 drug to achieve blood pressure goals. For specific advice on goals and management, see published guidelines, such as those of the National High Blood Pressure Education Program's Joint National Committee on Prevention, Detection, Evaluation, and Treatment of High Blood Pressure (JNC).

Numerous antihypertensive drugs, from a variety of pharmacologic classes and with different mechanisms of action, have been shown in randomized controlled trials to reduce cardiovascular morbidity and mortality, and it can be concluded that it is blood pressure reduction, and not some other pharmacologic property of the drugs, that is largely responsible for those benefits. The largest and most consistent cardiovascular outcome benefit has been a reduction in the risk of stroke, but reductions in myocardial infarction and cardiovascular mortality have also been seen regularly.

Elevated systolic or diastolic pressure causes increased cardiovascular risk, and the absolute risk increase per mmHg is greater at higher blood pressures, so that even modest reductions of severe hypertension can provide substantial benefit. Relative risk reduction from blood pressure reduction is similar across populations with varying absolute risk, so the absolute benefit is greater in patients who are at higher risk independent of their hypertension (e.g., patients with diabetes or hyperlipidemia), and such patients would be expected to benefit from more aggressive treatment to a lower blood pressure goal.

Some antihypertensive drugs have smaller blood pressure effects (as monotherapy) in black patients, and many antihypertensive drugs have additional approved indications and effects (e.g., on angina, heart failure, or diabetic kidney disease). These considerations may guide selection of therapy.

Add-On Therapy

A patient whose blood pressure is not adequately controlled with aliskiren alone or HCTZ alone may be switched to combination therapy with Tekturna HCT.

A patient whose blood pressure is controlled with HCTZ alone but who experiences hypokalemia may be switched to combination therapy with Tekturna HCT.

A patient who experiences dose-limiting adverse reactions on either component alone may be switched to Tekturna HCT containing a lower dose of that component in combination with the other to achieve similar blood pressure reductions.

Replacement Therapy

Tekturna HCT may be substituted for the titrated components.

Initial Therapy

Tekturna HCT may be used as initial therapy in patients who are likely to need multiple drugs to achieve their blood pressure goals.

The choice of Tekturna HCT as initial therapy should be based on an assessment of potential benefits and risks. Patients with Stage 2 hypertension are at a relatively high risk for cardiovascular events (such as strokes, heart attacks, and heart failure), kidney failure, and vision problems, so prompt treatment is clinically relevant. The decision to use a combination as initial therapy should be individualized and should be shaped by considerations such as baseline blood pressure, the target goal, and the incremental likelihood of achieving goal with a combination compared to monotherapy. Individual blood pressure goals may vary based upon the patient's risk.

Data from the high-dose multifactorial study [see Clinical Studies (14)] provide estimates of the probability of reaching a target blood pressure with Tekturna HCT compared to aliskiren or HCTZ monotherapy. Figures 1– 4 provide estimates of the likelihood of achieving systolic or diastolic blood pressure control with Tekturna HCT 300/25 mg, based upon baseline systolic or diastolic blood pressure. The curve of each treatment group was estimated by logistic regression modeling. The estimated likelihood at the right tail of each curve is less reliable because of small numbers of subjects with high baseline blood pressures.

Figure 1: Probability of Achieving Systolic Blood Pressure (SBP) Less Than 140 mmHg

Figure 2: Probability of Achieving Systolic Blood Pressure (SBP) Less Than 130 mmHg

Figure 3: Probability of Achieving Diastolic Blood Pressure (DBP) Less Than 90 mmHg

Figure 4: Probability of Achieving Diastolic Blood Pressure (DBP) Less Than 80 mmHg

At all levels of baseline blood pressure, the probability of achieving any given diastolic or systolic goal is greater with the combination than for either monotherapy. For example, the mean baseline msSBP/msDBP for patients participating in this multifactorial study was 154/99 mmHg. A patient with a baseline blood pressure of 154/99 mmHg has about a 62% chance of achieving a goal of less than 140 mmHg (systolic) and 61% chance of achieving less than 90 mmHg (diastolic) on aliskiren alone, and the chance of achieving these goals on HCTZ alone is about 54% (systolic) and 49% (diastolic). The chance of achieving these goals on Tekturna HCT rises to about 77% (systolic) and 74% (diastolic). The chance of achieving these goals on placebo is about 34% (systolic) and 37% (diastolic) [see Dosage and Administration (2) and Clinical Studies (14)].

2 DOSAGE AND ADMINISTRATION

2.1 Dose Selection

The recommended once-daily doses of Tekturna HCT in order of increasing mean effect are 150/12.5 mg, 150/25 mg or 300/12.5 mg, and 300/25 mg.

2.2 Dose Titration

The antihypertensive effect of Tekturna HCT is largely manifested within 1 week, with maximal effects generally seen at around 4 weeks. If blood pressure remains uncontrolled after 2 to 4 weeks of therapy, the dose may be titrated up to a maximum of aliskiren 300 mg/HCTZ 25 mg.

2.3 Add-On Therapy

A patient whose blood pressure is not adequately controlled with aliskiren alone or hydrochlorothiazide alone may be switched to combination therapy with Tekturna HCT. The usual recommended starting dose is 150/12.5 mg once daily as needed to control blood pressure. The dose may be titrated up to a maximum of aliskiren 300 mg/hydrochlorothiazide 25 mg once daily.

2.4 Replacement Therapy

Tekturna HCT may be substituted for the individually titrated components.

2.5 Initial Therapy

The usual recommended starting dose is 150/12.5 mg once daily as needed to control blood pressure. The dose may be titrated up to a maximum of aliskiren 300 mg/HCTZ 25 mg once daily.

Tekturna HCT is not recommended for use as initial therapy in patients with intravascular volume depletion [ see Warnings and Precautions (5.4) ].

2.6 Relationship to Meals

Patients should establish a routine pattern for taking Tekturna HCT with regard to meals. High-fat meals decrease absorption substantially [see Clinical Pharmacology (12.3)].

3 DOSAGE FORMS AND STRENGTHS

- 150 mg/12.5 mg tablets: white, biconvex ovaloid, film-coated tablets imprinted with NVR/LCI
- 150 mg/25 mg tablets: pale yellow, biconvex ovaloid, film-coated tablets imprinted with NVR/CLL
- 300 mg/12.5 mg tablets: violet white, biconvex ovaloid, film-coated tablets imprinted with NVR/CVI
- 300 mg/25 mg tablets: light yellow, biconvex ovaloid, film-coated tablets imprinted with NVR/CVV

4 CONTRAINDICATIONS

Do not use aliskiren with ARBs or ACEIs in patients with diabetes [see Warnings and Precautions (5.2) and Clinical Studies (14.4)].

Tekturna HCT is contraindicated in patients with known anuria or hypersensitivity to sulfonamide-derived drugs like HCTZ or to any of the components [see Warnings and Precautions (5.6) and Adverse Reactions (6.1)] . Hypersensitivity reactions may range from urticaria to anaphylaxis.

5 WARNINGS AND PRECAUTIONS

5.1 Fetal Toxicity

Aliskiren

Use of drugs that act on the renin-angiotensin system during the second and third trimesters of pregnancy reduces fetal renal function and increases fetal and neonatal morbidity and death. Resulting oligohydramnios can be associated with fetal lung hypoplasia and skeletal deformations. Potential neonatal adverse effects include skull hypoplasia, anuria, hypotension, renal failure, and death. When pregnancy is detected, discontinue Tekturna HCT as soon as possible [see Use in Specific Populations (8.1)].

Hydrochlorothiazide

Thiazides cross the placenta, and use of thiazides during pregnancy is associated with a risk of fetal or neonatal jaundice, thrombocytopenia, and possible other adverse reactions that have occurred in adults [see Use in Specific Populations (8.1)].

5.2 Renal Impairment/Hyperkalemia/Hypotension when Tekturna HCT is Given in Combination with ARBs or ACEIs

Tekturna HCT is contraindicated in patients with diabetes who are receiving ARBs or ACEIs because of the increased risk of renal impairment, hyperkalemia, and hypotension. In general, avoid combined use of aliskiren with ACE inhibitors or ARBs, particularly in patients with creatinine clearance (CrCl) less than 60 mL/min [see Contraindications (4), Drug Interactions (7) and Clinical Studies (14.3)] .

5.3 Anaphylactic Reactions and Head and Neck Angioedema

Aliskiren

Hypersensitivity reactions such as anaphylactic reactions and angioedema of the face, extremities, lips, tongue, glottis and/or larynx have been reported in patients treated with Tekturna and has necessitated hospitalization and intubation. This may occur at any time during treatment and has occurred in patients with and without a history of angioedema with ACEIs or angiotensin receptor antagonists. Anaphylactic reactions have been reported from postmarketing experience with unknown frequency. If angioedema involves the throat, tongue, glottis or larynx, or if the patient has a history of upper respiratory surgery, airway obstruction may occur and be fatal. Patients who experience these effects, even without respiratory distress, require prolonged observation and appropriate monitoring measures since treatment with antihistamines and corticosteroids may not be sufficient to prevent respiratory involvement. Prompt administration of subcutaneous epinephrine solution 1:1000 (0.3 mL to 0.5 mL) and measures to ensure a patent airway may be necessary.

Discontinue Tekturna HCT immediately in patients who develop anaphylactic reactions or angioedema, and do not readminister [see Contraindications (4)] .

5.4 Hypotension

Symptomatic hypotension may occur after initiation of treatment with Tekturna HCT in patients with marked volume depletion, patients with salt depletion, or with combined use of aliskiren and other agents acting on the renin-angiotensin-aldosterone system (RAAS). The volume or salt depletion should be corrected prior to administration of Tekturna HCT, or the treatment should start under close medical supervision.

A transient hypotensive response is not a contraindication to further treatment, which usually can be continued without difficulty once the blood pressure has stabilized.

5.5 Impaired Renal Function

Monitor renal function periodically in patients treated with Tekturna HCT. Changes in renal function, including acute renal failure, can be caused by drugs that affect the RAAS and by diuretics. Patients whose renal function may depend in part on the activity of the RAAS (e.g., patients with renal artery stenosis, severe heart failure, post-myocardial infarction or volume depletion) or patients receiving ARB, ACEI or nonsteroidal anti- inflammatory drug (NSAID), including selective Cyclooxygenase-2 inhibitors (COX-2 inhibitors), therapy may be at particular risk of developing acute renal failure on Tekturna HCT [see Warnings and Precautions (5.2), Drug Interactions (7), and Clinical Studies (14.4)] . Consider withholding or discontinuing therapy in patients who develop a clinically significant decrease in renal function on Tekturna HCT.

5.6 Hypersensitivity Reactions

Hydrochlorothiazide (HCTZ)

Hypersensitivity reactions to HCTZ may occur in patients with or without a history of allergy or bronchial asthma, but are more likely in patients with such a history.

5.7 Systemic Lupus Erythematosus

Hydrochlorothiazide (HCTZ)

Thiazide diuretics have been reported to cause exacerbation or activation of systemic lupus erythematosus.

5.8 Serum Electrolyte Abnormalities

Tekturna HCT

In the short-term controlled trials of various doses of Tekturna HCT, in patients with hypertension not concomitantly treated with an ARB or ACEI, the incidence of hypertensive patients who developed hypokalemia (serum potassium less than 3.5 mEq/L) was 2.2%; the incidence of hyperkalemia (serum potassium greater than 5.5 mEq/L) was 0.8%. No patients discontinued due to increase or decrease of serum potassium.

Aliskiren

Monitor serum potassium periodically in patients receiving aliskiren. Drugs that affect the RAAS can cause hyperkalemia. Risk factors for the development of hyperkalemia include renal insufficiency, diabetes, combination use with ARBs or ACEIs [see Contraindications (4), Warnings and Precautions (5.2), and Clinical Studies (14.4)], NSAIDs, including selective Cyclooxygenase-2 inhibitors (COX-2 inhibitors), or potassium supplements or potassium-sparing diuretics.

Hydrochlorothiazide (HCTZ)

HCTZ can cause hypokalemia and hyponatremia. Hypomagnesemia can result in hypokalemia which appears difficult to treat despite potassium repletion.

If hypokalemia is accompanied by clinical signs (e.g., muscular weakness, paresis, or ECG alterations), Tekturna HCT should be discontinued. Correction of hypokalemia and any coexisting hypomagnesemia is recommended prior to the initiation of thiazides.

5.9 Cyclosporine or Itraconazole

Aliskiren

When aliskiren was given with cyclosporine or itraconazole, the blood concentrations of aliskiren were significantly increased. Avoid concomitant use of aliskiren with cyclosporine or itraconazole [see Drug Interactions (7)] .

5.10 Acute Myopia and Secondary Angle-Closure Glaucoma

HCTZ, a sulfonamide, can cause an idiosyncratic reaction, resulting in acute transient myopia and acute angle- closure glaucoma. Symptoms include acute onset of decreased visual acuity or ocular pain and typically occur within hours to weeks of drug initiation. Untreated acute angle-closure glaucoma can lead to permanent vision loss. The primary treatment is to discontinue HCTZ as rapidly as possible. Prompt medical or surgical treatments may need to be considered if the intraocular pressure remains uncontrolled. Risk factors for developing acute angle-closure glaucoma may include a history of sulfonamide or penicillin allergy.

5.11 Metabolic Disturbances

Hydrochlorothiazide (HCTZ)

HCTZ may alter glucose tolerance and raise serum levels of cholesterol and triglycerides.

HCTZ may raise the serum uric acid level due to reduced clearance of uric acid and may cause or exacerbate hyperuricemia and precipitate gout in susceptible patients.

HCTZ decreases urinary calcium excretion and may cause elevations of serum calcium. Monitor calcium levels in patients with hypercalcemia receiving Tekturna HCT.

6 ADVERSE REACTIONS

6.1 Clinical Studies Experience

The following serious adverse reactions are discussed in greater detail in other sections of the label:

- Fetal Toxicity [see Warnings and Precautions (5.1)].
- Anaphylactic Reactions and Head and Neck Angioedema [see Warnings and Precautions (5.3)].
- Hypotension [see Warnings and Precautions (5.4)].

Because clinical trials are conducted under widely varying conditions, adverse reaction rates observed in the clinical trials of a drug cannot be directly compared to rates in clinical trials of another drug and may not reflect the rates observed in practice.

Tekturna HCT

Tekturna HCT has been evaluated for safety in more than 2,700 patients, including over 700 treated for 6 months and 190 for over 1 year. In placebo-controlled clinical trials, discontinuation of therapy due to a clinical adverse event (including uncontrolled hypertension) occurred in 2.7% of patients treated with Tekturna HCT versus 3.6% of patients given placebo.

Adverse events in placebo-controlled trials that occurred in at least 1% of patients treated with Tekturna HCT and at a higher incidence than placebo included dizziness (2.3% versus 1%), influenza (2.3% versus 1.6%), diarrhea (1.6% versus 0.5%), cough (1.3% versus 0.5%), vertigo (1.2% versus 0.5%), asthenia (1.2% versus 0%), and arthralgia (1% versus 0.5%).

Aliskiren

Aliskiren has been evaluated for safety in 6,460 patients, including 1,740 treated for longer than 6 months, and 1,250 for longer than 1 year. In placebo-controlled clinical trials, discontinuation of therapy due to a clinical adverse event, including uncontrolled hypertension occurred in 2.2% of patients treated with aliskiren, versus 3.5% of patients given placebo. These data do not include information from the ALTITUDE study which evaluated the use of aliskiren in combination with ARBs or ACEIs [see Contraindications (4), Warnings and Precautions (5.2), and Clinical Studies (14.4)].

Two cases of angioedema with respiratory symptoms were reported with aliskiren use in the clinical studies. Two other cases of periorbital edema without respiratory symptoms were reported as possible angioedema and resulted in discontinuation. The rate of these angioedema cases in the completed studies was 0.06%.

In addition, 26 other cases of edema involving the face, hands, or whole body were reported with aliskiren use, including 4 leading to discontinuation.

In the placebo-controlled studies, however, the incidence of edema involving the face, hands, or whole body was 0.4% with aliskiren compared with 0.5% with placebo. In a long-term active-controlled study with aliskiren and HCTZ arms, the incidence of edema involving the face, hands, or whole body was 0.4% in both treatment arms.

Aliskiren produces dose-related gastrointestinal (GI) adverse reactions. Diarrhea was reported by 2.3% of patients at 300 mg, compared to 1.2% in placebo patients. In women and the elderly (age 65 years and older) increases in diarrhea rates were evident starting at a dose of 150 mg daily, with rates for these subgroups at 150 mg comparable to those seen at 300 mg for men or younger patients (all rates about 2% to 2.3%). Other GI symptoms included abdominal pain, dyspepsia, and gastroesophageal reflux, although increased rates for abdominal pain and dyspepsia were distinguished from placebo only at 600 mg daily. Diarrhea and other GI symptoms were typically mild and rarely led to discontinuation.

Aliskiren was associated with a slight increase in cough in the placebo-controlled studies (1.1% for any aliskiren use versus 0.6% for placebo). In active-controlled trials with ACE inhibitor (ramipril, lisinopril) arms, the rates of cough for the aliskiren arms were about one-third to one-half the rates in the ACE inhibitor arms.

Other adverse reactions with increased rates for aliskiren compared to placebo included rash (1% versus 0.3%) and renal stones (0.2% versus 0%). Single episodes of tonic-clonic seizures with loss of consciousness were reported in 2 patients treated with aliskiren in the clinical trials. One patient had predisposing causes for seizures and had a negative electroencephalogram (EEG) and cerebral imaging following the seizures; for the other patient, EEG and imaging results were not reported. Aliskiren was discontinued and there was no rechallenge in either case.

No clinically meaningful changes in vital signs or in ECG (including QTc interval) were observed in patients treated with aliskiren.

Hydrochlorothiazide (HCTZ)

Other adverse reactions that have been reported with HCTZ, without regard to causality, are listed below:

Body As A Whole: weakness

Digestive: pancreatitis, jaundice (intrahepatic cholestatic jaundice), sialadenitis, cramping, gastric irritation

Hematologic: aplastic anemia, agranulocytosis, leukopenia, hemolytic anemia, thrombocytopenia;

Hypersensitivity: purpura, photosensitivity, urticaria, necrotizing angiitis (vasculitis and cutaneous vasculitis), fever, respiratory distress including pneumonitis and pulmonary edema, anaphylactic reactions

Metabolic: hyperglycemia, glycosuria, hyperuricemia

Musculoskeletal: muscle spasm

Nervous System/Psychiatric: restlessness

Renal: renal failure, renal dysfunction, interstitial nephritis

Skin: erythema multiforme including Stevens-Johnson syndrome, exfoliative dermatitis including toxic epidermal necrolysis

Special Senses: transient blurred vision, xanthopsia

Clinical Laboratory Test Abnormalities

In controlled clinical trials, clinically important changes in standard laboratory parameters were rarely associated with administration of Tekturna HCT in patients with hypertension not concomitantly treated with an ARB or ACEI.

Blood Urea Nitrogen (BUN)/Creatinine: In patients with hypertension not concomitantly treated with an ARB or ACEI, elevations (greater than 50% increase) in BUN and creatinine occurred in 11.8% and 0.9%, respectively, of patients taking Tekturna HCT, and 7% and 1.1%, respectively, of patients given placebo in short-term controlled clinical trials. No patients were discontinued due to an increase in either BUN or creatinine.

Hemoglobin and Hematocrit: A greater than 20% decrease in hemoglobin and hematocrit were observed in <0.1% and 0.1%, respectively, of patients treated with Tekturna HCT, compared with 0% in placebo-treated patients. No patients were discontinued due to anemia.

Liver Function Tests: Occasional elevations (greater than 150%) in ALT (SGPT) were observed in 1.2% of patients treated with Tekturna HCT, compared with 0% in placebo-treated patients. No patients were discontinued due to abnormal liver function tests.

6.2 Post-Marketing Experience

The following adverse reactions have been reported in aliskiren or hydrochlorothiazide post-marketing experience. Because these reactions are reported voluntarily from a population of uncertain size, it is not always possible to estimate their frequency or establish a causal relationship to drug exposure.

Aliskiren

Hypersensitivity: anaphylactic reactions and angioedema requiring airway management and hospitalization, urticaria, peripheral edema, hepatic enzyme increase with clinical symptoms of hepatic dysfunction, severe cutaneous adverse reactions, including Stevens-Johnson syndrome and toxic epidermal necrolysis, pruritus, erythema, hyponatremia , nausea, vomiting.

Hydrochlorothiazide

Acute renal failure, renal disorder, aplastic anemia, erythema mutliforme, pyrexia, muscle spasm, asthenia, acute angle-closure glaucoma, bone marrow failure, worsening of diabetes control, hypokalemia, blood lipids increased, hyponatremia, hypomagnesemia, hypercalcemia, hyperchloremic alkalosis, impotence, visual impairment.

Pathological changes in the parathyroid gland of patients with hypercalcemia and hypophosphatemia have been observed in a few patients on prolonged thiazide therapy. If hypercalcemia occurs, further diagnostic evaluation is necessary.

Non-melanoma Skin Cancer: Hydrochlorothiazide is associated with an increased risk of non-melanoma skin cancer. In a study conducted in the Sentinel System, increased risk was predominantly for squamous cell carcinoma (SCC) and in white patients taking large cumulative doses. The increased risk for SCC in the overall population was approximately 1 additional case per 16,000 patients per year, and for white patients taking a cumulative dose of ≥50,000mg the risk increase was approximately 1 additional SCC case for every 6,700 patients per year.

7 DRUG INTERACTIONS

No drug interaction studies have been conducted with Tekturna HCT and other drugs, although studies with the individual aliskiren and HCTZ components are described below.

Aliskiren

Cyclosporine: Avoid coadministration of cyclosporine with aliskiren [see Warnings and Precautions (5.9) and Clinical Pharmacology (12.3)] .

Itraconazole: Avoid coadministration of itraconazole with aliskiren [see Warnings and Precautions (5.7) and Clinical Pharmacology (12.3)].

Nonsteroidal Anti-Inflammatory Drugs (NSAIDs) including selective Cyclooxygenase-2 inhibitors (COX-2 inhibitors): In patients who are elderly, volume-depleted (including those on diuretic therapy), or with compromised renal function, coadministration of NSAIDs, including selective COX-2 inhibitors with agents that affect the RAAS, including aliskiren, may result in deterioration of renal function, including possible acute renal failure. These effects are usually reversible. Monitor renal function periodically in patients receiving aliskiren and NSAID therapy.

The antihypertensive effect of aliskiren may be attenuated by NSAIDs.

Dual Blockade of the Renin-Angiotensin-Aldosterone System (RAAS): The concomitant use of aliskiren with other agents acting on the RAAS such as ACEIs or ARBs is associated with an increased risk of hypotension, hyperkalemia, and changes in renal function (including acute renal failure) compared to monotherapy. Most patients receiving the combination of two drugs that inhibit the renin-angiotensin system do not obtain any additional benefit compared to monotherapy. In general, avoid combined use of aliskiren with ACE inhibitors or ARBs, particularly in patients with CrCl less than 60 mL/min. Monitor blood pressure, renal function, and electrolytes in patients on aliskiren and other agents that affect the RAAS [see Warnings and Precautions (5.4, 5.5, 5.8)].

The concomitant use of aliskiren with an ARB or an ACEI in diabetic patients is contraindicated [see Contraindications (4)].

Furosemide: Oral coadministration of aliskiren and furosemide reduced exposure to furosemide. Monitor diuretic effects when furosemide is coadministered with aliskiren.

Hydrochlorothiazide (HCTZ)

When administered concurrently, the following drugs may interact with thiazide diuretics.

Antidiabetic drugs (oral agents and insulin): Dosage adjustment of the antidiabetic drug may be required.

Lithium: Diuretic agents increase the risk of lithium toxicity. Increases in serum lithium concentrations and lithium toxicity have been reported during concomitant administration of lithium with angiotensin II receptor antagonists. Monitoring of serum lithium levels is recommended during concomitant use.

Nonsteroidal Anti-Inflammatory Drugs (NSAIDs) and COX-2 selective agents: When Tekturna HCT and NSAIDs are used concomitantly, the patient should be observed closely to determine if the desired effect of the diuretic is obtained.

Ion-exchange Resins: Staggering the dosage of HCTZ and ion exchange resins (e.g., cholestyramine, colestipol) such that HCTZ is administered at least 4 hours before or 4 to 6 hours after the administration of resins would potentially minimize the interaction [see Clinical Pharmacology (12.3)].

8 USE IN SPECIFIC POPULATIONS

8.1 Pregnancy

Risk Summary

Tekturna HCT can cause fetal harm when administered to a pregnant woman. Use of drugs that act on the renin- angiotensin system during the second and third trimesters of pregnancy reduces fetal renal function and increases fetal and neonatal morbidity and death. Most epidemiologic studies examining fetal abnormalities after exposure to antihypertensive use in the first trimester have not distinguished drugs affecting the renin- angiotensin system from other antihypertensive agents. When pregnancy is detected, discontinue Tekturna HCT as soon as possible.

The estimated background risk of major birth defects and miscarriage for the indicated population is unknown. All pregnancies have a background risk of birth defect, loss, or other adverse outcomes. In the U.S. general population, the estimated background risk of major malformations and miscarriage in clinically recognized pregnancies is 2-4%, and 15-20%, respectively.

Clinical Considerations

Disease-associated maternal and/or embryo/fetal risk

Hypertension in pregnancy increases the maternal risk for pre-eclampsia, gestational diabetes, premature delivery, and delivery complications (e.g., need for cesarean section, and post-partum hemorrhage). Hypertension increases the fetal risk for intrauterine growth restriction and intrauterine death. Pregnant women with hypertension should be carefully monitored and managed accordingly.

Fetal/Neonatal adverse reactions

Aliskiren

Use of drugs that act on the renin-angiotensin system in the second and third trimesters of pregnancy can result in the following: reduced fetal renal function leading to anuria and renal failure, oligohydramnios, fetal lung hypoplasia and skeletal deformations, including skull hypoplasia, hypotension, and death. In the unusual case that there is no appropriate alternative to therapy with drugs affecting the renin-angiotensin system for a particular patient, apprise the mother of the potential risk to the fetus.

In patients taking Tekturna HCT during pregnancy, perform serial ultrasound examinations to assess the intra-amniotic environment. Fetal testing may be appropriate, based on the week of gestation. Patients and physicians should be aware, however, that oligohydramnios may not appear until after the fetus has sustained irreversible injury. Closely observe infants with histories of in utero exposure to Tekturna HCT for hypotension, oliguria, and hyperkalemia. If oliguria or hypotension occur in neonates with a history of in utero exposure to Tekturna HCT, support blood pressure and renal perfusion Exchange transfusions or dialysis may be required as a means of reversing hypotension and substituting for disordered renal function.

Hydrochlorothiazide

Thiazides cross the placenta, and use of thiazides during pregnancy is associated with a risk of fetal or neonatal jaundice, thrombocytopenia, and possible other adverse reactions that have occurred in adults.

Data

Animal Data

No reproductive toxicity studies have been conducted with the combination of aliskiren and HCTZ. However, these studies have been conducted for aliskiren and HCTZ alone.

Aliskiren

In developmental toxicity studies, pregnant rats and rabbits received oral aliskiren hemifumarate during organogenesis at doses up to 20 and 7 times the maximum recommended human dose (MRHD) based on body surface area (mg/m^2), respectively, in rats and rabbits. (Actual animal doses were up to 600 mg/kg/day in rats and up to 100 mg/kg/day in rabbits.) No teratogenicity was observed; however, fetal birth weight was decreased in rabbits at doses 3.2 times the MRHD based on body surface area (mg/m^2). Aliskiren was present in placentas, amniotic fluid and fetuses of pregnant rabbits.

HCTZ

When pregnant mice and rats were given HCTZ at doses up to 3000 and 1000 mg/kg/day, respectively (about 600 and 400 times the MRHD), during their respective periods of major organogenesis, there was no evidence of fetal harm.

Thiazides can cross the placenta, and concentrations reached in the umbilical vein approach those in the maternal plasma. HCTZ, like other diuretics, can cause placental hypoperfusion. It accumulates in the amniotic fluid, with reported concentrations up to 19 times higher than in umbilical vein plasma. Use of thiazides during pregnancy is associated with a risk of fetal or neonatal jaundice or thrombocytopenia. Since they do not prevent or alter the course of EPH (Edema, Proteinuria, Hypertension) gestosis (pre eclampsia), these drugs should not be used to treat hypertension in pregnant women. The use of HCTZ for other indications (e.g., heart disease) in pregnancy should be avoided.

These animal studies were conducted according to the standards of the time.

8.2 Lactation

Risk Summary

There is no information regarding the presence of Tekturna HCT or aliskiren in human milk, the effects on the breastfed infant, or the effects on milk production. Limited published studies report that hydrochlorothiazide is present in human milk. However, there is insufficient information to determine the effects hydrochlorothiazide on the breastfed infant or the effects of hydrochlorothiazide on milk production. Because of the potential for serious adverse reactions, including hypotension, electrolyte imbalances and renal impairment in nursing infants, advise a nursing woman that breastfeeding is not recommended during treatment with Tekturna HCT.

8.4 Pediatric Use

Safety and effectiveness of Tekturna HCT in pediatric patients have not been established.

Preclinical studies indicate a potential for substantial increase in exposure to aliskiren in pediatric patients [see Nonclinical Toxicology (13.2)] .

Neonates with a history of in utero exposure to Tekturna HCT:

If oliguria or hypotension occurs, direct attention toward support of blood pressure and renal perfusion. Exchange transfusions or dialysis may be required as a means of reversing hypotension and/or substituting for disordered renal function.

8.5 Geriatric Use

In the short-term controlled clinical trials of Tekturna HCT, 325 (19.6%) patients treated with Tekturna HCT were 65 years and older and 53 (3.2%) were 75 years and older. No overall differences in safety or effectiveness were observed between these subjects and younger subjects, and other reported clinical experience has not identified differences in responses between the elderly and younger patients, but greater sensitivity of some older individuals cannot be ruled out.

8.6 Renal Impairment

Safety and effectiveness of Tekturna HCT in patients with severe renal impairment [creatinine clearance (CrCl) less than 30 mL/min] have not been established [see Warnings and Precautions (5.6), Clinical Pharmacology (12.3) and Clinical Studies (14)] .

No dose adjustment is required in patients with mild (CrCl 60 to 90 mL/min) or moderate (CrCl 30 to 60 mL/min) renal impairment.

8.7 Hepatic Impairment

Aliskiren

No dose adjustment is necessary for patients with mild-to-severe liver disease [see Clinical Pharmacology (12.3)].

Hydrochlorothiazide (HCTZ)

Minor alterations of fluid and electrolyte balance may precipitate hepatic coma in patients with impaired hepatic function or progressive liver disease.

10 OVERDOSAGE

Aliskiren

Limited data are available related to overdosage in humans. The most likely manifestation of overdosage would be hypotension. If symptomatic hypotension should occur, supportive treatment should be initiated.

Aliskiren is poorly dialyzed. Therefore, hemodialysis is not adequate to treat aliskiren overexposure [see Clinical Pharmacology (12.3)] .

Hydrochlorothiazide (HCTZ)

The most common signs and symptoms of overdose observed in humans are those caused by electrolyte depletion (hypokalemia, hypochloremia, hyponatremia) and dehydration resulting from excessive diuresis. If digitalis has also been administered, hypokalemia may accentuate cardiac arrhythmias. The degree to which HCTZ is removed by hemodialysis has not been established. The oral LD50 of HCTZ is greater than 10 g/kg in both mice and rats.

11 DESCRIPTION

Tekturna HCT is a fixed combination of aliskiren hemifumarate, an orally active, nonpeptide, direct renin inhibitor, and HCTZ, a thiazide diuretic that is provided as tablets for oral administration.

Aliskiren

Aliskiren hemifumarate is chemically described as (2S,4S,5S,7S)-N-(2-carbamoyl-2-methylpropyl)-5-amino-4- hydroxy-2,7-diisopropyl-8-[4-methoxy-3-(3-methoxypropoxy)phenyl]-octanamide hemifumarate and its structural formula is:

Molecular formula: C30H53N3O6 • 0.5 C4H4O4

Aliskiren hemifumarate is a white to slightly yellowish crystalline powder with a molecular weight of 609.8 (free base- 551.8). It is soluble in phosphate buffer, n-octanol, and highly soluble in water.

Hydrochlorothiazide (HCTZ)

Hydrochlorothiazide USP is a white, or practically white, practically odorless, crystalline powder. It is slightly soluble in water; freely soluble in sodium hydroxide solution, in n-butylamine, and in dimethylformamide; sparingly soluble in methanol; and insoluble in ether, in chloroform, and in dilute mineral acids.

Hydrochlorothiazide is chemically described as 6-chloro-3,4-dihydro-2 H-1,2,4-benzothiadiazine-7-sulfonamide 1,1-dioxide.

Hydrochlorothiazide is a thiazide diuretic. Its empirical formula is C7H8ClN3O4S2, its molecular weight is 297.73, and its structural formula is:

Tekturna HCT tablets are formulated for oral administration to contain aliskiren and hydrochlorothiazide, USP 150/12.5 mg, 150/25 mg, 300/12.5 mg, and 300/25 mg. The inactive ingredients for all strengths of the tablets are colloidal silicon dioxide, crospovidone, hydroxypropyl methylcellulose, iron oxide colorants, lactose, magnesium stearate, microcrystalline cellulose, polyethylene glycol, povidone, talc, titanium dioxide, and wheat starch.

12 CLINICAL PHARMACOLOGY

12.1 Mechanism of Action

Aliskiren

Renin is secreted by the kidney in response to decreases in blood volume and renal perfusion. Renin cleaves angiotensinogen to form the inactive decapeptide angiotensin I (Ang I). Ang I is converted to the active octapeptide angiotensin II (Ang II) by angiotensin-converting enzyme (ACE) and non-ACE pathways. Ang II is a powerful vasoconstrictor and leads to the release of catecholamines from the adrenal medulla and prejunctional nerve endings. It also promotes aldosterone secretion and sodium reabsorption. Together, these effects increase blood pressure. Ang II also inhibits renin release, thus providing a negative feedback to the system. This cycle, from renin through angiotensin to aldosterone and its associated negative feedback loop, is known as the renin-angiotensin-aldosterone system (RAAS). Aliskiren is a direct renin inhibitor, decreasing plasma renin activity (PRA) and inhibiting the conversion of angiotensinogen to Ang I. Whether aliskiren affects other RAAS components, e.g., ACE or non-ACE pathways, is not known.

All agents that inhibit the RAAS, including renin inhibitors, suppress the negative feedback loop, leading to a compensatory rise in plasma renin concentration. When this rise occurs during treatment with ACE inhibitors and ARBs, the result is increased levels of PRA. During treatment with aliskiren, however, the effect of increased renin levels is blocked, so that PRA, Ang I and Ang II are all reduced, whether aliskiren is used as monotherapy or in combination with other antihypertensive agents.

Hydrochlorothiazide (HCTZ)

HCTZ is a thiazide diuretic. Thiazides affect the renal tubular mechanisms of electrolyte reabsorption, directly increasing excretion of sodium and chloride in approximately equivalent amounts. Indirectly, the diuretic action of HCTZ reduces plasma volume, with consequent increases in plasma renin activity, increases in aldosterone secretion, increases in urinary potassium loss, and decreases in serum potassium. The renin-aldosterone link is mediated by angiotensin II, so coadministration of agents that block the production or function of angiotensin II tends to reverse the potassium loss associated with these diuretics.

The mechanism of action of the antihypertensive effect of thiazides is unknown.

12.2 Pharmacodynamics

Tekturna HCT

In placebo-controlled clinical trials, PRA was decreased with aliskiren monotherapy (ranging from 54% to 65%) and increased with hydrochlorothiazide monotherapy (ranging from 4% to 72%). Treatment with Tekturna HCT resulted in PRA reductions ranging from approximately 46% to 63% in various doses despite the increase in PRA with hydrochlorothiazide treatment. The clinical implications of the differences in effect on PRA are not known.

Aliskiren

PRA reductions in clinical trials ranged from approximately 50% to 80%, were not dose-related and did not correlate with blood pressure reductions. The clinical implications of the differences in effect on PRA are not known.

Hydrochlorothiazide (HCTZ)

After oral administration of HCTZ, diuresis begins within 2 hours, peaks in about 4 hours, and lasts about 6 to 12 hours.

Drug Interactions

Hydrochlorothiazide (HCTZ)

Alcohol, barbiturates, or narcotics: Potentiation of orthostatic hypotension may occur.

Skeletal muscle relaxants: Possible increased responsiveness to muscle relaxants such as curare derivatives.

Digitalis glycosides: Thiazide-induced hypokalemia or hypomagnesemia may predispose the patient to digoxin toxicity.

12.3 Pharmacokinetics

Absorption and Distribution

Tekturna HCT

Following oral administration of Tekturna HCT combination tablets, the median peak plasma concentration time is within 1 hour for aliskiren and 2.5 hours for HCTZ. When taken with food, mean AUC and Cmax of aliskiren are decreased by 60% and 82%, respectively; mean AUC and Cmax of HCTZ increased by 13% and 10%, respectively. As a result, patients should establish a routine pattern for taking Tekturna HCT with regard to meals.

Aliskiren

Aliskiren is poorly absorbed (bioavailability about 2.5%). Following oral administration, peak plasma concentrations of aliskiren are reached within 1 to 3 hours. When taken with a high fat meal, mean AUC and Cmax of aliskiren are decreased by 71% and 85% respectively. In the clinical trials of aliskiren, it was administered without requiring a fixed relation of administration to meals.

Hydrochlorothiazide (HCTZ)

The estimated absolute bioavailability of HCTZ after oral administration is about 70%. Peak plasma HCTZ concentrations (Cmax) are reached within 2 to 5 hours after oral administration. There is no clinically significant effect of food on the bioavailability of HCTZ.

HCTZ binds to albumin (40% to 70%) and distributes into erythrocytes. Following oral administration, plasma HCTZ concentrations decline bi-exponentially, with a mean distribution half-life of about 2 hours and an elimination half-life of about 10 hours.

Metabolism and Elimination

Aliskiren

The effective half-life for aliskiren is 24 hours. Steady state blood levels are reached in about 7 to 8 days. About one-fourth of the absorbed dose appears in the urine as parent drug. How much of the absorbed dose is metabolized is unknown. Based on the in vitro studies, the major enzyme responsible for aliskiren metabolism appears to be CYP3A4. Aliskiren does not inhibit the CYP450 isoenzymes (CYP 1A2, 2C8, 2C9, 2C19, 2D6, 2E1, and 3A) or induce CYP3A4.

Transporters: Pgp (MDR1/Mdr1a/1b) was found to be the major efflux system involved in intestinal absorption and elimination via biliary excretion of aliskiren in preclinical studies. The potential for drug interactions at the Pgp site will likely depend on the degree of inhibition of this transporter.

Hydrochlorothiazide (HCTZ)

About 70% of an orally administered dose of HCTZ is eliminated in the urine as unchanged drug.

Drug Interactions:

Aliskiren

The effect of coadministered drugs on the pharmacokinetics of aliskiren and vice versa, were studied in several single and multiple dose studies. Pharmacokinetic measures indicating the magnitude of these interactions are presented in Figure 5 (impact of coadministered drugs on aliskiren) and Figure 6 (impact on coadministered drugs).

Figure 5: The Impact of Coadministered Drugs on the Pharmacokinetics of Aliskiren

*Ketoconazole: A 400 mg once daily dose was not studied, but would be expected to increase aliskiren blood levels further.

**Ramipril, valsartan, irbesartan: In general, avoid combined use of aliskiren with ACE inhibitors or ARBs, particularly in patients with CrCl less than 60 mL/min [see Drug Interactions (7)].

Warfarin: There was no clinically significant effect of a single dose of warfarin 25 mg on the pharmacokinetics of aliskiren.

Figure 6: The Impact of Aliskiren on the Pharmacokinetics of Coadministered Drugs

* Furosemide: Patients receiving furosemide may find its effects diminished after starting aliskiren. In patients with heart failure, co-administration of aliskiren (300 mg/day) reduced plasma AUC and Cmax of oral furosemide (60 mg/day) by 17% and 27%, respectively, and reduced 24 hour urinary furosemide excretion by 29%. This change in exposure did not result in statistically significant difference in total urine volume and urinary sodium excretion over 24 hours. However, a transient decrease in urinary sodium excretion and urine volume effects up to 12 hours were observed when furosemide was co-administered with aliskiren 300 mg/day.

**Ramipril, valsartan: In general, avoid combined use of aliskiren with ACE inhibitors or ARBs, particularly in patients with CrCl less than 60 mL/min [see Drug Interactions (7)].

Hydrochlorothiazide (HCTZ)

Drugs that alter gastrointestinal motility: The bioavailability of thiazide-type diuretics may be increased by anticholinergic agents (e.g., atropine, biperiden), apparently due to a decrease in gastrointestinal motility and the stomach emptying rate. Conversely, pro-kinetic drugs may decrease the bioavailability of thiazide diuretics.

Cholestyramine: In a dedicated drug interaction study, administration of cholestyramine 2 hours before HCTZ resulted in a 70% reduction in exposure to HCTZ. Further, administration of HCTZ 2 hours before cholestyramine, resulted in 35% reduction in exposure to HCTZ.

Antineoplastic agents (e.g., cyclophosphamide, methotrexate): Concomitant use of thiazide diuretics may reduce renal excretion of cytotoxic agents and enhance their myelosuppressive effects.

Special Populations

Pediatric Patients

The pharmacokinetics of aliskiren have not been investigated in patients less than 18 years of age.

Geriatric Patients

Aliskiren

The pharmacokinetics of aliskiren were studied in the elderly (65 years and older). Exposure (measured by AUC) is increased in elderly patients.

Hydrochlorothiazide (HCTZ)

A limited amount of data suggest that the systemic clearance of HCTZ is reduced in both healthy and hypertensive elderly subjects compared to young healthy volunteers.

Race

Too few non-Caucasians have been studied with Tekturna HCT to assess pharmacokinetic differences among races. The pharmacokinetic differences among blacks, Caucasians, and Japanese are minimal with aliskiren therapy.

Renal Impairment

Aliskiren

The pharmacokinetics of aliskiren were evaluated in patients with varying degrees of renal impairment. Rate and extent of exposure (AUC and Cmax) of aliskiren in subjects with renal impairment did not show a consistent correlation with the severity of renal impairment [see Use in Specific Populations (8.6)].

The pharmacokinetics of aliskiren following administration of a single oral dose of 300 mg was evaluated in patients with End Stage Renal Disease (ESRD) undergoing hemodialysis. When compared to matched healthy subjects, changes in the rate and extent of aliskiren exposure (Cmax and AUC) in ESRD patients undergoing hemodialysis were not clinically significant.

Timing of hemodialysis did not significantly alter the pharmacokinetics of aliskiren in ESRD patients. Therefore, no dose adjustment is warranted in ESRD patients receiving hemodialysis.

Hydrochlorothiazide (HCTZ)

In a study in individuals with impaired renal function, the mean elimination half-life of HCTZ was doubled in individuals with mild/moderate renal impairment (30 < CrCl < 90 mL/min) and tripled in severe renal impairment (CrCl less than or equal to 30 mL/min), compared to individuals with normal renal function (CrCl greater than 90 mL/min) [see Use in Specific Populations (8.6)] .

Hepatic Impairment

Aliskiren

The pharmacokinetics of aliskiren were not significantly affected in patients with mild-to-severe liver disease [see Use in Specific Populations (8.7)] .

13 NONCLINICAL TOXICOLOGY

13.1 Carcinogenesis, Mutagenesis, Impairment of Fertility

Tekturna HCT

No carcinogenicity, mutagenicity or fertility studies have been conducted with Tekturna HCT. However, these studies have been conducted for aliskiren as well as HCTZ alone.

Aliskiren

Carcinogenic potential was assessed in a 2-year rat study and a 6-month transgenic (rasH2) mouse study with aliskiren hemifumarate at oral doses of up to 1500 mg aliskiren/kg/day. Although there were no statistically significant increases in tumor incidence associated with exposure to aliskiren, mucosal epithelial hyperplasia with or without erosion/ulceration) was observed in the lower gastrointestinal tract at doses of 750 or more mg/kg/day in both species, with a colonic adenoma identified in 1 rat and a cecal adenocarcinoma identified in another, rare tumors in the strain of rat studied. On a systemic exposure (AUC0-24hr) basis, 1500 mg/kg/day in the rat was about 4 times and in the mouse about 1.5 times the MRHD (300 mg aliskiren/day). Mucosal hyperplasia in the cecum or colon of rats was also observed at doses of 250 mg/kg/day (the lowest tested dose) as well as at higher doses in 4- and 13-week studies.

Aliskiren hemifumarate was devoid of genotoxic potential in the Ames reverse mutation assay with S. typhimurium and E. coli, the in vitro Chinese hamster ovary cell chromosomal aberration assay, the in vitro Chinese hamster V79 cell gene mutation test and the in vivo mouse bone marrow micronucleus assay.

Fertility of male and female rats was unaffected at doses of up to 250 mg aliskiren/kg/day (8 times the MRHD of 300 mg Tekturna/60 kg on a mg/m^2 basis).

Hydrochlorothiazide (HCTZ)

Two-year feeding studies in mice and rats conducted under the auspices of the National Toxicology Program (NTP) uncovered no evidence of a carcinogenic potential of HCTZ in female mice (at doses of up to approximately 600 mg/kg/day) or in male and female rats (at doses of up to approximately 100 mg/kg/day). The NTP, however, found equivocal evidence for hepatocarcinogenicity in male mice.

HCTZ was not genotoxic in vitro in the Ames mutagenicity assay of S. typhimurium strains TA 98, TA 100, TA 1535, TA 1537, and TA 1538 and in the Chinese Hamster Ovary (CHO) test for chromosomal aberrations, or in vivo in assays using mouse germinal cell chromosomes, Chinese hamster bone marrow chromosomes, and the Drosophila sex-linked recessive lethal trait gene. Positive test results were obtained only in the in vitro CHO Sister Chromatid Exchange (clastogenicity) and in the Mouse Lymphoma Cell (mutagenicity) assays, using concentrations of HCTZ from 43 to 1300 mcg/mL, and in the Aspergillums Nidulans nondisjunction assay at an unspecified concentration.

HCTZ was not teratogenic and had no adverse effects on the fertility of mice and rats of either sex in studies wherein these species were exposed, via their diet, to doses of up to 100 and 4 mg/kg, respectively, prior to mating and throughout gestation. These doses of HCTZ in mice and rats represent 19 and 1.5 times, respectively, the MRHD on a mg/m^2 basis. (Calculations assume an oral dose of 25 mg/day and a 60-kg patient.)

13.2 Animal Toxicology and/or Pharmacology

Reproductive Toxicology Studies

[See Use in Specific Populations (8.1).]

Juvenile Animal Studies

Juvenile toxicity studies indicated increased systemic exposure to aliskiren 85- to 385-fold in 14 day and 8 day old rats respectively, compared with adult rats. The mdr1 gene expression in juvenile rats was also significantly lower when compared to adult rats. The increased aliskiren exposure in juvenile rats appears to be mainly attributed to lack of maturation of P-gp. The overexposure in juvenile rats was associated with high mortality [see Use in Specific Populations (8.4)] .

14 CLINICAL STUDIES

14.1 Tekturna HCT

In all clinical trials including over 6,200 patients, more than 2,700 patients were exposed to combinations of aliskiren and HCTZ. The safety and efficacy of Tekturna HCT were evaluated in patients with mild-to-moderate hypertension in an 8-week, randomized, double-blind, placebo-controlled, parallel-group, 15-arm factorial trial (n=2762). Patients were randomized to receive various combinations of aliskiren (75 mg to 300 mg) plus HCTZ (6.25 mg to 25 mg) once daily (without titrating up from monotherapy) and followed for blood pressure response. The combination of aliskiren and HCTZ resulted in additive placebo-adjusted decreases in systolic and diastolic blood pressure at trough of 10–14/5–7 mmHg at doses of 150–300 mg/12.5–25 mg, compared to 5–8/2–3 mmHg for aliskiren 150 mg to 300 mg and 6–7/2–3 mmHg for HCTZ 12.5 mg to 25 mg, alone. Blood pressure reductions with the combinations were greater than the reductions with the monotherapies as shown in Table 1.

Table 1: Placebo-Subtracted Reductions in Seated Trough Cuff Blood Pressure in Combination with Hydrochlorothiazide (HCTZ)
 |  | Hydrochlorothiazide, mg
 |  | 0 | 6.25 | 12.5 | 25
Aliskiren, mg | Placebo Mean Change | Placebo- subtracted | Placebo- subtracted | Placebo- subtracted | Placebo- subtracted
0 | 7.5/6.9 | -- | 3.5/2.1 | 6.4/3.2 | 6.8/2.4
75 | -- | 1.9/1.8 | 6.8/3.8 | 8.2/4.2 | 9.8/4.5
150 | -- | 4.8/2 | 7.8/3.4 | 10.1/5 | 12/5.7
300 | -- | 8.3/3.3 | -- | 12.3/7 | 13.7/7.3

The safety and efficacy of Tekturna HCT as initial therapy was evaluated in this trial. All patients randomized to the combination groups received the combination treatment of Tekturna HCT at assigned doses as initial therapy without titration from monotherapy. The figures [see Indications and Usage (1)] display the probability that a patient will achieve systolic or diastolic blood pressure goal with Tekturna HCT 300/25 mg, based upon their baseline systolic or diastolic blood pressure. At all levels of baseline blood pressure, the probability of achieving any given diastolic or systolic goal is greater with the combination than for either monotherapy.

The antihypertensive effect of Tekturna HCT was largely manifested within 1 week. The maximum antihypertensive effect was generally attained after about 4 weeks of therapy.

One active-controlled trial investigated the addition of 300 mg aliskiren in obese hypertensive patients who did not respond adequately to HCTZ 25 mg, and showed incremental decreases of systolic and diastolic blood pressure of approximately 7/4 mmHg.

In long-term follow-up studies (without placebo control) the effect of the combination of aliskiren and HCTZ was maintained for over 1 year.

The antihypertensive effect was independent of age and gender. There were too few non-Caucasians to assess differences in blood pressure effects by race.

14.2 Aliskiren Monotherapy

The antihypertensive effects of aliskiren have been demonstrated in 6 randomized, double-blind, placebo- controlled, 8-week clinical trials in patients with mild-to-moderate hypertension. The placebo response and placebo-subtracted changes from baseline in seated trough cuff blood pressure are shown in Table 2.

Table 2: Reductions in Seated Trough Cuff Blood Pressure in the Placebo-Controlled Studies of Aliskiren Monotherapy
 |  | Aliskiren Daily Dose, mg
 |  | 75 | 150 | 300 | 600
Study | Placebo Mean Change | Placebo-subtracted | Placebo-subtracted | Placebo-subtracted | Placebo-subtracted
1 | 2.9/3.3 | 5.7/4* | 5.9/4.5* | 11.2/7.5* | --
2 | 5.3/6.3 | -- | 6.1/2.9* | 10.5/5.4* | 10.4/5.2*
3 | 10/8.6 | 2.2/1.7 | 2.1/1.7 | 5.1/3.7* | --
4 | 7.5/6.9 | 1.9/1.8 | 4.8/2* | 8.3/3.3* | --
5 | 3.8/4.9 | -- | 9.3/5.4* | 10.9/6.2* | 12.1/7.6*
6 | 4.6/4.1 | -- | -- | 8.4/4.9† | --
*p value less than 0.05 versus placebo by ANCOVA with Dunnett's procedure for multiple comparisons.
†p value less than 0.05 versus placebo by ANCOVA for the pairwise comparison.

The studies included approximately 2,730 patients given doses of 75 mg to 600 mg of aliskiren and 1,231 patients given placebo. As shown in Table 2, there is some increase in response with administered dose in all studies, with reasonable effects seen at 150 mg to 300 mg, and no clear further increase at 600 mg. A substantial proportion (85% to 90%) of the blood pressure lowering effect was observed within 2 weeks of treatment.

Studies with ambulatory blood pressure monitoring showed reasonable control throughout the interdosing interval, e.g., the ratios of mean daytime to mean nighttime ambulatory BP ranged from 0.6 to 0.9.

Patients in the placebo-controlled trials continued open-label aliskiren for up to 1 year. A persistent blood pressure lowering effect was demonstrated by a randomized withdrawal study (patients randomized to continued drug or placebo), which showed a statistically significant difference between patients kept on aliskiren and those randomized to placebo. With cessation of treatment, blood pressure gradually returned toward baseline levels over a period of several weeks. There was no evidence of rebound hypertension after abrupt cessation of therapy.

The effectiveness of aliskiren was demonstrated across all demographic subgroups, although black patients tended to have smaller reductions in blood pressure than Caucasians and Asians, as has been seen with ACE inhibitors and ARBs.

14.3 Aliskiren in Combination with Other Antihypertensives

Valsartan

Aliskiren 150 mg and 300 mg and valsartan 160 mg and 320 mg were studied alone and in combination in an 8- week, 1,797-patient, randomized, double-blind, placebo-controlled, parallel-group, 4-arm, dose-escalation study. The dosages of aliskiren and valsartan were started at 150 mg and 160 mg, respectively, and increased at 4 weeks to 300 mg and 320 mg, respectively. Seated trough cuff blood pressure was measured at baseline, 4, and 8 weeks. Blood pressure reductions with the combinations were greater than the reductions with the monotherapies as shown in Table 3. In general, avoid use of aliskiren in combination with other drugs that affect the RAAS [see Contraindications (4), Warnings and Precautions (5), and Drug Interactions (7)] .

Table 3: Placebo-Subtracted Reductions in Seated Trough Cuff Blood Pressure of Aliskiren in Combination with Valsartan
 |  | Valsartan, mg
Aliskiren, mg | Placebo Mean Change | 0 | 160 | 320
0 | 4.6/4.1* | -- | 5.6/3.9 | 8.2/5.6
150 | -- | 5.4/2.7 | 10.0/5.7 | --
300 | -- | 8.4/4.9 | -- | 12.6/8.1
* The placebo change is 5.2/4.8 for Week 4 endpoint which was used for the dose groups containing aliskiren 150 mg or valsartan 160 mg.

Amlodipine

Aliskiren 150 mg and 300 mg and amlodipine besylate 5 mg and 10 mg were studied alone and in combination in an 8- week, 1,685-patient, randomized, double-blind, placebo-controlled, multifactorial study. Treatment with aliskiren and amlodipine resulted overall in significantly greater reductions in diastolic and systolic blood pressure compared to the respective monotherapy components as shown in Table 4.

Table 4: Placebo-Subtracted Reductions in Seated Trough Cuff Blood Pressure in Combination with Amlodipine
Aliskiren, mg | Placebo mean change | Amlodipine, mg
Aliskiren, mg | Placebo mean change | 0 | 5 | 10
0 | 5.4/6.8 | -- | 5.6/9.0 | 8.5/14.3
150 | -- | 2.6/3.9 | 8.6/13.9 | 10.8/17.1
300 | -- | 4.9/8.6 | 9.6/15.0 | 11.1/16.4

ACEIs

Aliskiren has not been studied when added to maximal doses of ACEIs to determine whether aliskiren produces additional blood pressure reduction.

There are no trials of the Tekturna HCT combination tablet demonstrating reductions in cardiovascular risk in patients with hypertension, but the HCTZ component has demonstrated such benefits.

14.4 Aliskiren in Patients with Diabetes Treated with an ARB or ACEI (ALTITUDE study)

Patients with diabetes with renal disease (defined either by the presence of albuminuria or reduced GFR) were randomized to aliskiren 300 mg daily (n=4296) or placebo (n=4310). All patients were receiving background therapy with an ARB or ACEI. The primary efficacy outcome was the time to the first event of the primary composite endpoint consisting of cardiovascular death, resuscitated sudden death, nonfatal myocardial infarction, nonfatal stroke, unplanned hospitalization for heart failure, onset of end stage renal disease, renal death, and doubling of serum creatinine concentration from baseline sustained for at least 1 month. After a median follow up of about 32 months, the trial was terminated early for lack of efficacy. Higher risk of renal impairment, hypotension and hyperkalemia was observed in aliskiren compared to placebo treated patients, as shown in Table 5.

Table 5: Incidence of Selected Adverse Events During the Treatment Phase in ALTITUDE
 | Aliskiren N=4272 |  | Placebo N=4285
 | Serious Adverse Events* (%) | Adverse Events (%) | Serious Adverse Events* (%) | Adverse Events (%)
Renal impairment † | 5.7 | 14.5 | 4.3 | 12.4
Hypotension †† | 2.3 | 19.9 | 1.9 | 16.3
Hyperkalemia ††† | 1.0 | 38.9 | 0.5 | 28.8
†renal failure, renal failure acute, renal failure chronic, renal impairment
††dizziness, dizziness postural, hypotension, orthostatic hypotension, presyncope, syncope
††† Given the variable baseline potassium levels of patients with renal insufficiency on dual RAAS therapy, the reporting of adverse event of hyperkalemia was at the discretion of the investigator.
* A Serious Adverse Event (SAE) is defined as: an event which is fatal or life-threatening, results in persistent or significant disability/incapacity, constitutes a congenital anomaly/birth defect, requires inpatient hospitalization or prolongation of existing hospitalization, or is medically significant (i.e., defined as an event that jeopardizes the patient or may require medical or surgical intervention to prevent one of the outcomes previously listed).

The risk of stroke (3.4% aliskiren versus 2.7% placebo) and death (8.4% aliskiren versus 8.0% placebo) were also numerically higher in aliskiren-treated patients.

16 HOW SUPPLIED/STORAGE AND HANDLING

Tekturna HCT is supplied as biconvex, ovaloid film-coated tablets.

All strengths are packaged in bottles and unit-dose blister packages (10 strips of 10 tablets) as described below.

Table 6: Tekturna HCT Tablets Supply
Tablet | Color | Imprint | Imprint | NDC 70839-XXX-XX
Aliskiren/HCTZ |  | Side 1 | Side 2 | Bottle of 30 | Bottle of 90 | Blister Packages of 100
150 mg/12.5 mg | White | NVR | LCI | 112-30 | 112-90 | 112-01
150 mg/25 mg | Pale Yellow | NVR | CLL | 125-30 | 125-90 | 125-01
300 mg/12.5 mg | Violet White | NVR | CVI | 312-30 | 312-90 | 312-01
300 mg/25 mg | Light Yellow | NVR | CVV | 325-30 | 325-90 | 325-01

Storage

Store at 25ºC (77ºF); excursions permitted to 15ºC to 30ºC (59ºF to 86ºF) [See USP Controlled Room Temperature].

Protect from moisture. Dispense in original container.

17 PATIENT COUNSELING INFORMATION

Advise the patient to read the FDA-approved patient labeling (Patient Information).

Pregnancy

Inform female patients of childbearing age about the consequences of exposure to Tekturna HCT during pregnancy. Discuss treatment options with women planning to become pregnant. Advise patients to report pregnancies to their physicians as soon as possible.

Lactation

Advise nursing women that breastfeeding is not recommended during treatment with Tekturna HCT [see Use in Specific Populations (8.2)].

Symptomatic Hypotension

Inform patients that lightheadedness can occur, especially during the first days of Tekturna HCT therapy, and that it should be reported to the prescribing physician. Advise patients that if syncope occurs, Tekturna HCT should be discontinued until the physician has been consulted.

Caution patients that inadequate fluid intake, excessive perspiration, diarrhea, or vomiting can lead to an excessive fall in blood pressure, with the same consequences of lightheadedness and possible syncope.

Anaphylactic Reactions and Angioedema

Advise patients to immediately report any signs or symptoms suggesting a severe allergic reaction (difficulty breathing or swallowing, tightness of the chest, hives, general rash, swelling, itching, dizziness, vomiting, or abdominal pain) or angioedema (swelling of face, extremities, eyes, lips, tongue, difficulty in swallowing or breathing) and to take no more drug until they have consulted with the prescribing physician. Angioedema, including laryngeal edema, may occur at any time during treatment with Tekturna HCT.

Potassium Supplements

Advise patients receiving Tekturna HCT not to use potassium supplements or salt substitutes containing potassium without consulting the prescribing physician.

Relationship to Meals

Instruct patients to establish a routine pattern for taking Tekturna HCT with regard to meals. High-fat meals decrease absorption substantially.

Non-melanoma Skin Cancer: Instruct patients taking hydrochlorothiazide to protect skin from the sun and undergo regular skin cancer screening.

Patient Information

Tekturna® HCT (tek-turn-a HCT)
(aliskiren and hydrochlorothiazide)
Tablets

Read the Patient Information that comes with Tekturna HCT before you start taking it and each time you get a refill. There may be new information. This leaflet does not take the place of talking with your doctor about your condition and treatment.

What is the most important information I should know about Tekturna HCT?

Tekturna HCT can cause harm or death to an unborn baby. Talk to your doctor about other ways to lower your blood pressure if you plan to become pregnant. If you get pregnant while taking Tekturna HCT, tell your doctor right away.

What is Tekturna HCT?

Tekturna HCT contains 2 prescription medicines in 1 tablet that work together to lower blood pressure. It contains:

- aliskiren (Tekturna), a direct renin inhibitor (DRI)
- hydrochlorothiazide (HCTZ), a diuretic (water pill)

Aliskiren (Tekturna) reduces the effect of renin, and the harmful process that narrows blood vessels. Aliskiren also helps blood vessels relax and widen so blood pressure is lower. Hydrochlorothiazide reduces the amount of salt and water in your body so your blood pressure is lower.

Tekturna HCT may be used to lower high blood pressure in adults

- when 1 medicine to lower high blood pressure is not enough
- as the first medicine to lower high blood pressure if your doctor decides that you are likely to need more than 1 medicine

Tekturna HCT has not been studied in children under 18 years of age.

Your doctor may prescribe other medicines for you to take along with Tekturna HCT to treat your high blood pressure.

What is high blood pressure (hypertension)?

Blood pressure is the force of blood in your blood vessels when your heart beats and when your heart rests. You have high blood pressure when the force is too much.

High blood pressure makes the heart work harder to pump blood throughout the body and causes damage to blood vessels. Tekturna HCT can help your blood vessels relax so your blood pressure is lower. Medicines that lower your blood pressure may lower your chance of having a stroke or heart attack.

Who should not take Tekturna HCT?

Do not take Tekturna HCT if:

- you get pregnant. Stop taking Tekturna HCT and call your doctor right away. If you plan to become pregnant, talk to your doctor about other treatment options for your high blood pressure.
- you have diabetes and are taking a kind of medicine called an angiotensin receptor blocker (ARB) or angiotensin-converting enzyme inhibitor (ACEI).
- you make very little or no urine due to kidney problems.
- you are allergic to aliskiren, hydrochlorothiazide, any of the other ingredients of Tekturna HCT listed at the end of this leaflet.
- Tekturna HCT has not been studied in children under 18 years of age

What should I tell my doctor before taking Tekturna HCT?

Before taking Tekturna HCT, tell your doctor if you:

- have kidney problems
- are pregnant or planning to become pregnant. See “What is the most important information I should know about Tekturna HCT?”
- have any allergies or asthma
- have liver problems
- have systemic lupus erythematosus (SLE). Tekturna HCT can make your SLE active or worse.
- have ever had an allergic reaction called angioedema, to another blood pressure medicine. Symptoms may include swelling of the face, lips, tongue, throat,arms, and legs, and may cause difficulty breathing (angioedema).
- are breastfeeding. It is not known if Tekturna HCT passes into your breast milk and if it can harm your baby.
- have any other medical problems

Tell your doctor about all the medicines you take, including prescription and nonprescription medicines, vitamins and herbal supplements. Tekturna HCT and certain other medicines may affect each other and cause side effects.

Especially tell your doctor if you are taking:

- a kind of medicine to control blood pressure called angiotensin receptor blocker (ARB) or angiotensin-converting enzyme inhibitor (ACEI)
- cholesterol-lowering medicines
  - simvastatin (Zocor®) or atorvastatin (Lipitor®)
  - cholestyramine (Questran, Questran Light, Cholestyramine Light, Locholest Light, Locholest, Prevalite)
  - colestipol (Colestipol hydrochloride, Colestid, Flavored Colestid)
- medicines used to lower blood pressure, water pills (also called “diuretics”), especially potassium-sparing diuretics
- medicines for treating fungus or fungal infections (like itraconazole or ketoconazole)
- cyclosporine (Gengraf®, Neoral, Sandimmune), a medicine used to suppress the immune system
- potassium-containing medicines, potassium supplements, or salt substitutes containing potassium
- medicines used to treat diabetes, including insulin
- lithium, a medicine used in some types of depression
- medicines used to relieve pain or inflammation, especially nonsteroidal anti- inflammatory drugs (NSAIDs) (like ibuprofen or naproxen), including selective Cyclooxygenase-2-inhibitors (COX-2 inhibitors). Ask your doctor if you are not sure if you are taking one of these medicines.

Ask your doctor if you are not sure whether you are taking one of the medicines listed above. Know the medicines you take. Keep a list of them to show your doctor or pharmacist when you get a new medicine. Your doctor or pharmacist will know what medicines are safe to take together.

How should I take Tekturna HCT?

- Take Tekturna HCT exactly as prescribed by your doctor. It is important to take Tekturna HCT every day to control your blood pressure.
- Take Tekturna HCT once each day, about the same time each day.
- Take Tekturna HCT the same way every day, either with or without a meal.
- Your doctor may change your dose of Tekturna HCT if needed.
- If you miss a dose of Tekturna HCT, take it as soon as you remember. If it is close to your next dose, do not take the missed dose. Just take the next dose at your regular time.
- If you take too much Tekturna HCT, call your doctor or a Poison Control Center, or go to the nearest hospital emergency room.

What should I avoid while taking Tekturna HCT?

Drinking alcohol. Drinking alcohol during treatment with Tekturna HCT can cause you to have low blood pressure. See “ What are the possible side effects of Tekturna HCT?”

What are the possible side effects of Tekturna HCT?

Tekturna HCT may cause serious side effects:

- Harm to an unborn baby, causing injury or death. See “ What is the most important information I should know about Tekturna HCT?”
- Severe Allergic Reactions and Angioedema (hypersensitivity). Aliskiren, one of the medicines in Tekturna HCT, can cause difficulty breathing or swallowing, tightness of the chest, hives, general rash, swelling, itching, dizziness, vomiting, or abdominal pain (signs of a severe allergic reaction called anaphylactic reaction). Aliskiren can also cause swelling of the face, lips, tongue, throat, arms and legs, or the whole body (signs of angioedema). Stop taking Tekturna HCT and get medical help right away. Tell your doctor if you get any one or more of these symptoms. Angioedema can happen at any time while you are taking Tekturna HCT.
- Low blood pressure (hypotension). Your blood pressure may get too low if you also take water pills, are on a low-salt diet, get dialysis treatments, have heart problems, or get sick with vomiting or diarrhea. Drinking alcohol and taking certain medicines (barbiturates or narcotics) can cause low blood pressure to get worse. Lie down if you feel faint or dizzy, and call your doctor right away.
- Renal Impairment or Failure. Aliskiren, one of the medicines in Tekturna HCT, may cause renal disorder with symptoms such as severely decreased urine output or decreased urine output (signs of renal impairment or failure).
- Tekturna HCT may affect your potassium levels. Your doctor will do blood tests to check your potassium levels.
- Allergic reactions: Hydrochlorothiazide, one of the medicines in Tekturna HCT, can cause allergic reactions.
- Active or Worsened Systemic Lupus Erythematosus (SLE). If you have SLE, tell your doctor right away if you get any new or worse symptoms. Possible signs of SLE are facial rash, joint pain, muscle disorder, fever.
- Eye problems. One of the medicines in Tekturna HCT can cause eye problems that may lead to vision loss. Symptoms of eye problems can happen within hours to weeks of starting Tekturna HCT. Tell your doctor right away if you have:
  - Decrease in vision
  - Eye pain

Common side effects of Tekturna HCT include:

- dizziness
- flu-like symptoms
- diarrhea
- cough
- tiredness
- high levels of potassium in the blood (hyperkalemia)
- vertigo
- arthralgia

Less common side effects include skin rash, severe skin reactions (signs may include severe blistering of the lips, eyes or mouth, rash with fever and skin peeling), liver disorder (signs may include nausea, loss of appetite, dark colored urine or yellowing of skin and eyes) and low level of sodium in blood.

Protect your skin from the sun and undergo regular skin cancer screening, as one of the medicines in Tekturna HCT may cause non-melanoma skin cancer.

Tell your doctor if you have any side effect that bothers you or that does not go away. These are not all of the possible side effects of Tekturna HCT. For a complete list of side effects, ask your doctor or pharmacist.

Call your doctor for medical advice about side effects. You may report side effects to FDA at 1-800-FDA-1088.

How do I store Tekturna HCT?

- Store Tekturna HCT tablets at room temperature between 59°F to 86°F (15°C to 30°C).
- Keep Tekturna HCT in the original prescription bottle in a dry place. Do not remove the desiccant (drying agent) from the bottle.

Keep Tekturna HCT and all medicines out of the reach of children.

General information about Tekturna HCT

Medicines are sometimes prescribed for conditions not listed in the patient information leaflet. Do not take Tekturna HCT for a condition for which it was not prescribed. Do not give Tekturna HCT to other people, even if they have the same condition or symptoms you have. It may harm them.

This leaflet summarizes the most important information about Tekturna HCT. If you have questions about Tekturna HCT talk with your doctor or pharmacist. You can ask your doctor or pharmacist for information that is written for healthcare professionals.

For more information about Tekturna HCT, visit www.Tekturna.com, or call 1-844-399-5701.

What are the ingredients in Tekturna HCT?

Active ingredients: aliskiren hemifumarate and hydrochlorothiazide Inactive ingredients: colloidal silicon dioxide, crospovidone, hydroxypropyl methylcellulose, iron oxide colorants, lactose, magnesium stearate, microcrystalline cellulose, polyethylene glycol, povidone, talc, titanium dioxide, and wheat starch.

Distributed by:

NODEN PHARMA USA INC
2800 Discovery Drive, Suite 100,
Orlando, FL 32826

© 2020 Noden Pharma USA Inc. All rights reserved.

September 2020

PACKAGE LABEL

Principal Display Panel - Tekturna HCT 150/12.5 mg Label

NDC 70839-112-30 30 tablets

Tekturna HCT®

(aliskiren and hydrochlorothiazide)

Tablets

150 mg/12.5 mg

Rx only

NODEN PHARMA™

PACKAGE LABEL

Principal Display Panel - Tekturna HCT 150/25 mg Label

NDC 70839-125-30 30 tablets

Tekturna HCT®

(aliskiren and hydrochlorothiazide)

Tablets

150 mg/25 mg

Rx only

NODEN PHARMA™

PACKAGE LABEL

Principal Display Panel - Tekturna HCT 300/12.5 mg Label

NDC 70839-312-30 30 tablets

Tekturna HCT®

(aliskiren and hydrochlorothiazide)

Tablets

300 mg/12.5 mg

Rx only

NODEN PHARMA™

PACKAGE LABEL

Principal Display Panel - Tekturna HCT 300/25 mg Label

NDC 70839-325-30 30 tablets

Tekturna HCT®

(aliskiren and hydrochlorothiazide)

Tablets

300 mg/25 mg

Rx only

NODEN PHARMA™